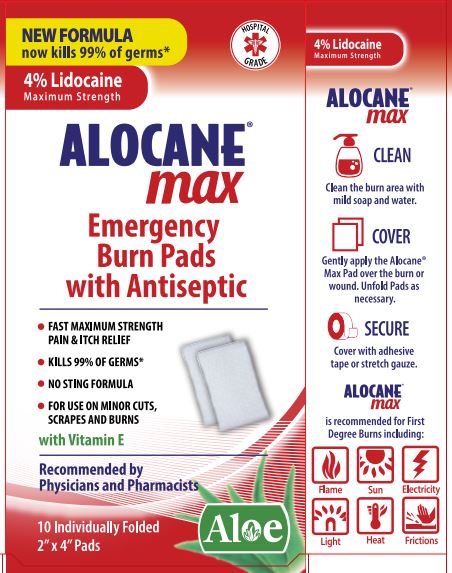 DRUG LABEL: Alocane Max
NDC: 68229-407 | Form: LIQUID
Manufacturer: Quest Products LLC
Category: otc | Type: HUMAN OTC DRUG LABEL
Date: 20241105

ACTIVE INGREDIENTS: LIDOCAINE HYDROCHLORIDE 4 g/100 mL; BENZALKONIUM CHLORIDE 0.13 g/100 mL
INACTIVE INGREDIENTS: PROPANEDIOL; ALOE VERA LEAF; DIMETHYL ISOSORBIDE; HYDROXYETHYL CELLULOSE (5500 MPA.S AT 2%); PHENOXYETHANOL; CAPRYLYL GLYCOL; CHLORPHENESIN; .ALPHA.-TOCOPHEROL ACETATE; WATER

Alocane® Max Burn Pads

Drug Facts

ACTIVE INGREDIENT

Active Ingredient | Purpose
Benzalkonium Chloride 0.13%; Lidocaine HCL 4% | First Aid Antiseptic; Topical Analgesic

Uses:

First aid to help prevent bacterial contamination or skin infection, and for temporary relief or pain and itching associated with minor:

- Burns
- Cuts
- Sunburn
- Scrapes
- Minor Skin Irritations

Warnings

For External Use Only.

Ask a doctor before use if you have:

- Deep or puncture wounds
- Animal Bites
- Serious burns

Do not use:

- In or near the eyes
- In large quantities or over large areas of the body
- On raw surfaces or blistered areas

Stop use and ask doctor: if condition worsens, or if symptoms persist for more than 7 days or clear up and occur again within a few days.

PREGNANCY OR BREAST FEEDING

If pregnant or breast-feeding, ask a health care professional before use.

Keep out of reach of children. If swallowed, get medical help or call a Poison Control Center right away.

Directions

Adults and children 2 years of age and older: Clean affected area and let dry. Gently apply the Burn Pad over the burn or wound. Cover with adhesive tape or stretch gauze. Use on affected area not more than 3 or 4 times daily.

Children under 2 years of age: ask a doctor.

Other Information

Store at room temperature 15°-30°C (59°-86°F)

Inactive Ingredients

1,3-Propanediol, Aloe Barbadensis (Aloe) Leaf Juice, Caprylyl Glycol, Chlorphenesin, Dimethyl Isosorbide, Hydroxyethyl Cellulose, Phenoxyethanol, Tocopheryl Acetate (Vitamin E), Water.